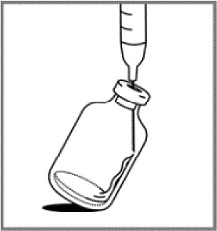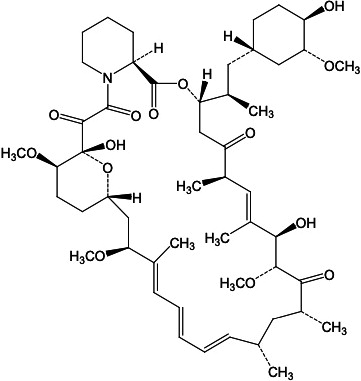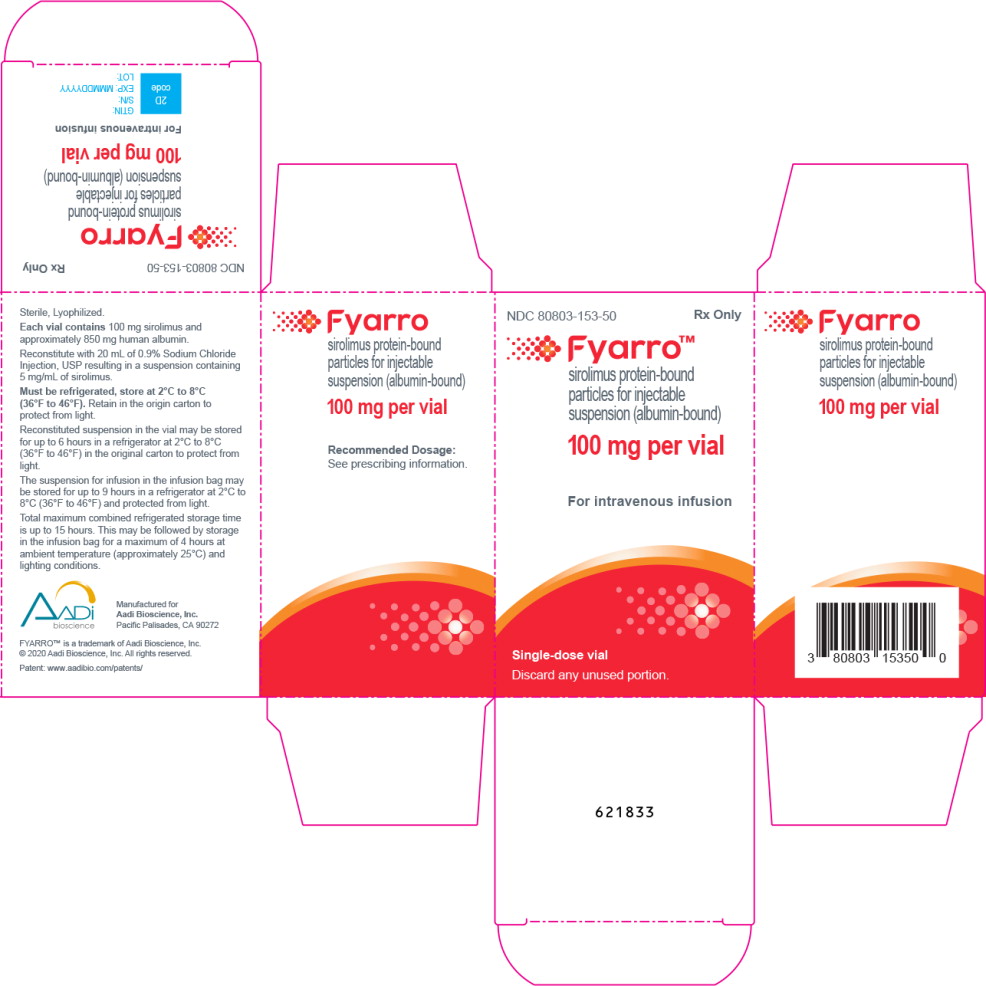 DRUG LABEL: FYARRO
NDC: 80803-153 | Form: INJECTION, POWDER, LYOPHILIZED, FOR SUSPENSION
Manufacturer: Aadi Bioscience, Inc.
Category: prescription | Type: HUMAN PRESCRIPTION DRUG LABEL
Date: 20260204

ACTIVE INGREDIENTS: SIROLIMUS 5 mg/1 mL
INACTIVE INGREDIENTS: ALBUMIN HUMAN

HIGHLIGHTS OF PRESCRIBING INFORMATION

These highlights do not include all the information needed to use FYARRO safely and effectively. See full prescribing information for FYARRO.
FYARRO™ (sirolimus protein-bound particles for injectable suspension) (albumin-bound), for intravenous use
Initial U.S. Approval: 2021

1 INDICATIONS AND USAGE

- FYARRO is an mTOR inhibitor indicated for the treatment of adult patients with locally advanced unresectable or metastatic malignant perivascular epithelioid cell tumor (PEComa). (1)

2 DOSAGE AND ADMINISTRATION

- The recommended dosage of FYARRO is 100 mg/m^2 administered as an IV infusion over 30 minutes on Days 1 and 8 of each 21-day cycle until disease progression or unacceptable toxicity. (2.1)

3 DOSAGE FORMS AND STRENGTHS

- For injectable suspension: lyophilized powder containing 100 mg of sirolimus formulated as albumin-bound particles in single-dose vial for reconstitution. (3)

4 CONTRAINDICATIONS

- History of severe hypersensitivity to sirolimus, other rapamycin derivatives, or albumin. (4)

5 WARNINGS AND PRECAUTIONS

- Stomatitis: Withhold, resume at reduced dose, or permanently discontinue based on severity. (5.1)
- Myelosuppression: Monitor blood counts prior to and during FYARRO treatment as clinically indicated. Withhold, resume at reduced dose, or permanently discontinue based on severity. (5.2)
- Infections: May result from immunosuppression. Monitor for signs and symptoms of infection. Withhold, resume at reduced dose, or permanently discontinue based on severity. (5.3)
- Hypokalemia and hyperglycemia: Monitor serum potassium and glucose prior to starting FYARRO and as clinically indicated. Withhold, resume at reduced dose, or permanently discontinue based on severity. (5.4, 5.5)
- ILD/Non-Infectious Pneumonitis: Monitor for new or worsening respiratory symptoms or radiological changes. Withhold, resume at reduced dose, or permanently discontinue based on severity. (5.6)
- Hemorrhage: Monitor for signs and symptoms. Withhold, resume at reduced dose, or permanently discontinue based on severity. (5.7)
- Hypersensitivity Reactions: Monitor for hypersensitivity during and following each FYARRO infusion. Monitor for at least 2 hours following completion of the first infusion and as clinically indicated for each subsequent infusion. Reduce the rate, interrupt infusion, or permanently discontinue based on severity. (5.8)
- Embryo-Fetal Toxicity: Can cause fetal harm. Advise patients of the potential hazard to the fetus and to use effective contraception. (5.9)
- Male Infertility: Azoospermia or oligospermia may occur. (5.10)
- Immunizations: Avoid live vaccines (5.11)

6 ADVERSE REACTIONS

The most common (≥30%) adverse reactions were stomatitis, fatigue, rash, infection, nausea, edema, diarrhea, musculoskeletal pain, decreased weight, decreased appetite, cough, vomiting, and dysgeusia. (6.1)

The most common (≥6%) Grade 3 to 4 laboratory abnormalities were decreased lymphocytes, increased glucose, decreased potassium, decreased phosphate, decreased hemoglobin, and increased lipase. (6.1)

To report SUSPECTED ADVERSE REACTIONS, contact Aadi Bioscience, Inc. at 1-888-BIO-AADI (888-246-2234) or FDA at 1-800-FDA-1088 or www.fda.gov/medwatch.

7 DRUG INTERACTIONS

- Strong CYP3A4 and/or P-gp Inhibitors or Inducers: Avoid concomitant use. (2.3, 7.1)
- Moderate or Weak CYP3A4 Inhibitors: Reduce FYARRO dose. (2.3, 7.1)

8 USE IN SPECIFIC POPULATIONS

- Hepatic Impairment: Reduce the dose of FYARRO in patients with mild or moderate hepatic impairment. Avoid use in patients with severe hepatic impairment. (2.4, 8.6)
- Lactation: Advise not to breastfeed. (8.2)
- Females and Males of Reproductive Potential: May impair fertility in females and males. (5.9, 5.10, 8.3)

FULL PRESCRIBING INFORMATION

1 INDICATIONS AND USAGE

FYARRO™ is indicated for the treatment of adult patients with locally advanced unresectable or metastatic malignant perivascular epithelioid cell tumor (PEComa).

2 DOSAGE AND ADMINISTRATION

2.1 Recommended Dosage

The recommended dosage of FYARRO is 100 mg/m2 administered as an intravenous infusion over 30 minutes on Days 1 and 8 of each 21-day cycle until disease progression or unacceptable toxicity.

2.2 Dosage Modifications for Adverse Reactions

Table 1 lists the recommended dose reductions of FYARRO for adverse reactions.

Table 1. Recommended dose reductions of FYARRO for adverse reactions.
Dose Reduction | Dose
First Dose Reduction | 75 mg/m^2 (25% reduction from 100 mg/m^2)
Second Dose Reduction | 56 mg/m^2 (25% reduction from 75 mg/m^2)
Third Dose Reduction [Permanently discontinue FYARRO in patients who are unable to tolerate FYARRO after three dose reductions.] | 45 mg/m^2 (20% reduction from 56 mg/m^2)

Table 2 lists the recommended dosage modifications of FYARRO for adverse reactions.

Table 2. Recommended FYARRO Dosage Modifications for Adverse Reactions
Adverse Reaction | Severity [Severity based on Common Terminology Criteria for Adverse Events Version 4.03.] | Dosage Modifications
Stomatitis [see Warnings and Precautions (5.1)] | Grade 2 or 3 | - Withhold FYARRO until Grade ≤1. - Restart at the same dose for first occurrence. - If recurs, restart at reduced dose level.
Stomatitis [see Warnings and Precautions (5.1)] | Grade 4 | - Permanently discontinue FYARRO.
Anemia [see Warnings and Precautions (5.2)] | Grade 2 | - Withhold FYARRO until Hb ≥8 g/dL. - Restart at the same dose level.
Anemia [see Warnings and Precautions (5.2)] | Grade ≥3 | - Withhold FYARRO until Hb ≥8 g/dL. - Restart at the same dose level. - If recurs, resume at reduced dose level.
Thrombocytopenia [see Warnings and Precautions (5.2)] | Grade 2 | - Withhold FYARRO until platelet count >100×10^9/L. - Restart at the same dose level.
Thrombocytopenia [see Warnings and Precautions (5.2)] | Grade ≥3 | - Withhold FYARRO until platelet count >100×10^9/L. - Restart at reduced dose level.
Neutropenia [see Warnings and Precautions (5.2)] | Grade 2 or 3 | - Withhold FYARRO until absolute neutrophil count ≥1.5×10^9/L. - Restart at the same dose level.
Neutropenia [see Warnings and Precautions (5.2)] | Grade 4 | - Withhold FYARRO until absolute neutrophil count ≥1.5×10^9/L. - Restart at reduced dose level.
Infections [see Warnings and Precautions (5.3)] | Grade 3 | - Withhold FYARRO until resolved. - Restart at reduced dose level. - If recurs, permanently discontinue FYARRO.
Infections [see Warnings and Precautions (5.3)] | Grade 4 | - Withhold FYARRO until resolved. - Restart at reduced dose level or permanently discontinue FYARRO.
Hypokalemia [see Warnings and Precautions (5.4)] | Grade 2 | - Withhold FYARRO until Grade ≤1. - Restart at the same dose level. - If recurs, restart at reduced dose level.
Hypokalemia [see Warnings and Precautions (5.4)] | Grade ≥3 | - Withhold FYARRO until Grade ≤1. - Restart at reduced dose level. - If recurs, permanently discontinue FYARRO.
Hyperglycemia [see Warnings and Precautions (5.5)] | Grade ≥3 | - Withhold FYARRO until Grade ≤2. - Restart at reduced dose level.
Interstitial Lung Disease / Non- Infectious Pneumonitis [see Warnings and Precautions (5.6)] | Grade 2 | - Withhold FYARRO for up to 3 weeks until Grade ≤1. - Restart at reduced dose level. - If not resolved to Grade ≤1 within 3 weeks, permanently discontinue FYARRO. - If recurs, permanently discontinue FYARRO.
Interstitial Lung Disease / Non- Infectious Pneumonitis [see Warnings and Precautions (5.6)] | Grade ≥3 | - Permanently discontinue FYARRO.
Hemorrhage [see Warnings and Precautions (5.7)] | Grade 2 or 3 | - Withhold FYARRO until Grade ≤1. - Resume at reduced dose. - If recurs, permanently discontinue FYARRO.
Hemorrhage [see Warnings and Precautions (5.7)] | Grade 4 | - Permanently discontinue FYARRO.
Other Adverse Reactions [see Adverse Reactions (6.1)] | Grade 3 | - Withhold FYARRO until Grade ≤1. - Restart at the same dose level. - If recurs, restart at reduced dose level.
Other Adverse Reactions [see Adverse Reactions (6.1)] | Grade 4 | - Permanently discontinue FYARRO.

2.3 Dosage Modifications for Concomitant Use with CYP3A4 and/or P-gp Inhibitors and Inducers

Reduce the dosage of FYARRO to 56 mg/m^2 when used concomitantly with a moderate or weak cytochrome P-450 3A4 (CYP3A4) inhibitor. Avoid concomitant use with drugs that are strong CYP3A4 and/or P-glycoprotein (P-gp) inhibitors and inducers and with grapefruit and grapefruit juice [see Drug Interactions (7.1), Clinical Pharmacology (12.3)].

2.4 Patients with Hepatic Impairment

The recommended dosage modification of FYARRO in patients with mild or moderate hepatic impairment is described in Table 3 [see Use in Specific Populations (8.6), Clinical Pharmacology (12.3)]. Closely monitor patients with hepatic impairment for increased toxicity. Avoid use in patients with severe hepatic impairment [see Use in Specific Populations (8.6)].

Table 3. Recommended FYARRO Dosage in Patients with Mild or Moderate Hepatic Impairment
Hepatic Impairment (based on NCI criteria) | Dosage
Mild (total bilirubin ≤ULN, AST >ULN or total bilirubin >1 to 1.5×ULN, any AST) | 75 mg/m^2
Moderate (total bilirubin >1.5 to 3.0×ULN, any AST) | 56 mg/m^2

2.5 Preparation and Administration

FYARRO is a hazardous drug. Follow applicable special handling and disposal procedures.^1

FYARRO is supplied as a sterile lyophilized powder for reconstitution before use. READ ENTIRE PREPARATION INSTRUCTIONS PRIOR TO RECONSTITUTION.

Preparation:

1. Aseptically, reconstitute each vial by injecting 20 mL of 0.9% Sodium Chloride Injection, USP.

2. Slowly inject the 20 mL of 0.9% Sodium Chloride Injection, USP, over a minimum of 1 minute, using the sterile syringe to direct the solution flow onto the INSIDE WALL OF THE VIAL.

3. DO NOT INJECT the 0.9% Sodium Chloride Injection, USP, directly on to the lyophilized powder, which has a cake-like appearance, as this will result in foaming.

4. Once the injection is complete, allow the vial to sit for a minimum of 5 minutes to ensure proper wetting of the lyophilized powder.

5. Gently swirl and/or invert the vial slowly for at least 2 minutes until complete dissolution of any powder occurs. Avoid shaking the vial to prevent the generation of foam.

6 .If foaming or clumping occurs, let suspension stand for at least 15 minutes until foam subsides. If foaming or clumping is present after one hour, do not use the reconstituted suspension.

Each mL of the reconstituted formulation will contain 5 mg sirolimus.

The reconstituted suspension should be milky and homogenous without visible particulates. If particulates or settling are visible, the vial should be gently inverted again to ensure complete resuspension prior to use. Discard the reconstituted suspension if precipitates are observed. Discard any unused portion.

7. Transfer the volume of FYARRO required for the calculated dose into an empty sterile PVC or polyolefin infusion bag for administration without further dilution.

The use of medical devices containing silicone oil as a lubricant (e.g., syringes and intravenous bags) to reconstitute and administer FYARRO may result in the formation of proteinaceous strands.

Visually inspect reconstituted FYARRO suspension in the infusion bag prior to administration. Discard reconstituted suspension if particulate matter, proteinaceous strands, or discoloration are observed.

Administration:

Administer the reconstituted FYARRO suspension intravenously over 30 minutes.

2.6 Stability

Unopened vials of FYARRO are stable until the date indicated on the package when stored between 2°C to 8°C (36°F to 46°F) in the original package. Neither freezing nor thawing adversely affects the stability of the product.

Stability of Reconstituted Suspension in the Vial

Reconstituted FYARRO in the vial should be used immediately but may be refrigerated at 2°C to 8°C (36°F to 46°F) for a maximum of 6 hours stored in the original carton to protect it from light. Discard any unused portion.

Stability of Reconstituted Suspension in the Infusion Bag

The suspension for infusion when prepared as recommended in an infusion bag should be used immediately but may be refrigerated at 2°C to 8°C (36°F to 46°F) and protected from light for a maximum of 9 hours.

The total maximum combined refrigerated storage time of reconstituted FYARRO in the vial and in the infusion bag is 15 hours. This may be followed by storage in the infusion bag at ambient temperature (approximately 25°C) and lighting conditions for a maximum of 4 hours. Discard any unused portion.

3 DOSAGE FORMS AND STRENGTHS

For injectable suspension: white to yellow, sterile lyophilized powder containing 100 mg of sirolimus formulated as albumin-bound particles in single-dose vial for reconstitution.

4 CONTRAINDICATIONS

FYARRO is contraindicated in patients with a history of severe hypersensitivity to sirolimus, other rapamycin derivatives, or albumin [see Warnings and Precautions (5.8)].

5 WARNINGS AND PRECAUTIONS

5.1 Stomatitis

Stomatitis, including mouth ulcers and oral mucositis, occurred in 79% of patients treated with FYARRO, including 18% Grade 3. Stomatitis was most often first reported within 8 weeks of treatment. Based on the severity of the adverse reaction, withhold, resume at reduced dose, or permanently discontinue FYARRO [see Dosage and Administration (2.2), Adverse Reactions (6.1)]

5.2 Myelosuppression

FYARRO can cause myelosuppression including anemia, thrombocytopenia and neutropenia. Anemia occurred in 68% of patients; 6% were Grade 3. Thrombocytopenia and neutropenia occurred in 35% of patients each.

Obtain blood counts at baseline and every 2 months for the first year of treatment and every 3 months thereafter, or more frequently if clinically indicated. Based on the severity of the adverse reaction, withhold, resume at reduced dose, or permanently discontinue FYARRO [see Dosage and Administration (2.2), Adverse Reactions (6.1)].

5.3 Infections

FYARRO can cause infections. Infections such as urinary tract infections (UTI), upper respiratory tract infections and sinusitis occurred in 59% of patients. Grade 3 infections occurred in 12% of patients, including a single case each of a UTI, pneumonia, skin, and abdominal infections. Monitor patients for infections, including opportunistic infections. Based on the severity of the adverse reaction, withhold, resume at reduced dose, or permanently discontinue FYARRO [see Dosage and Administration (2.2), Adverse Reactions (6.1)].

5.4 Hypokalemia

FYARRO can cause hypokalemia. Hypokalemia occurred in 44% of patients, including 12% Grade 3 events. Monitor potassium levels prior to starting FYARRO and implement potassium supplementation as medically indicated. Based on the severity of the adverse reaction, withhold, resume at reduced dose, or permanently discontinue FYARRO [see Dosage and Administration (2.2), Adverse Reactions (6.1)].

5.5 Hyperglycemia

FYARRO can cause hyperglycemia. Hyperglycemia occurred in 12% of patients treated with FYARRO, all of which were Grade 3 events. Monitor fasting serum glucose prior to starting FYARRO. During treatment, monitor serum glucose every 3 months in non-diabetic patients, or as clinically indicated. Monitor serum glucose more frequently in diabetic patients. Based on the severity of the adverse reaction, withhold, resume at reduced dose, or permanently discontinue FYARRO [see Dosage and Administration (2.2), Adverse Reactions (6.1)].

5.6 Interstitial Lung Disease / Non-Infectious Pneumonitis

FYARRO can cause interstitial lung disease (ILD) / non-infectious pneumonitis. ILD / non-infectious pneumonitis occurred in 18% of patients treated with FYARRO, of which all were Grades 1 or 2. Based on the severity of the adverse reaction, withhold, resume at reduced dose, or permanently discontinue FYARRO [see Dosage and Administration (2.2)].

5.7 Hemorrhage

FYARRO can cause serious and sometimes fatal hemorrhage. Hemorrhage occurred in 24% of patients treated with FYARRO, including Grade 3 and Grade 5 events in 2.9% of patients each [see Adverse Reactions (6.1)]. Monitor patients for signs and symptoms of hemorrhage. Based on the severity of the adverse reaction, withhold, resume at reduced dose, or permanently discontinue FYARRO [see Dosage and Administration (2.2)].

5.8 Hypersensitivity Reactions

FYARRO can cause hypersensitivity reactions [see Contraindications (4)].

- Hypersensitivity reactions, including anaphylactic, angioedema, exfoliative dermatitis and hypersensitivity vasculitis have been observed with administration of the oral formulation of sirolimus.
- Hypersensitivity reactions including anaphylaxis have been observed with human albumin administration.

Monitor patients closely for signs and symptoms of infusion reactions during and following each FYARRO infusion in a setting where cardiopulmonary resuscitation medication and equipment are available. Monitor patients for at least 2 hours after the first infusion and as clinically needed for each subsequent infusion.

Reduce the rate, interrupt infusion, or permanently discontinue FYARRO based on severity and institute appropriate medical management as needed.

5.9 Embryo-Fetal Toxicity

Based on animal studies and the mechanism of action [see Clinical Pharmacology (12.1)], FYARRO can cause fetal harm when administered to a pregnant woman. In animal studies, mechanistic target of rapamycin kinase (mTOR) inhibitors caused embryo-fetal toxicity when administered during the period of organogenesis at maternal exposures that were equal to or less than human exposures at the recommended lowest starting dose. Advise pregnant women of the potential risk to a fetus. Advise females of reproductive potential to avoid becoming pregnant and to use effective contraception while using FYARRO and for 12 weeks after the last dose [see Use in Specific Populations (8.1, 8.3)].

5.10 Male Infertility

Azoospermia or oligospermia may be observed in patients treated with FYARRO [see Use in Specific Populations (8.3), Nonclinical Toxicology (13.1)]. FYARRO is an anti-proliferative drug and affects rapidly dividing cells such as germ cells.

5.11 Immunizations and Risks Associated with Live Vaccines

No studies in conjunction with immunization have been conducted with FYARRO. Immunization during FYARRO treatment may be ineffective. Update immunizations according to immunization guidelines prior to initiating FYARRO, if possible. Immunization with live vaccines is not recommended during treatment and avoid close contact with those who have received live vaccines while on FYARRO. The interval between live vaccinations and initiation of FYARRO should be in accordance with current vaccination guidelines for patients on immunosuppressive therapies.

5.12 Risk of Transmission of Infectious Agents with Human Albumin

FYARRO contains human albumin, a derivative of human blood. Human albumin carries only a remote risk of transmission of viral diseases because of effective donor screening and product manufacturing processes. A theoretical risk for transmission of Creutzfeldt-Jakob Disease (CJD) also is considered extremely remote. No cases of transmission of viral diseases or CJD have ever been associated with albumin.

6 ADVERSE REACTIONS

The following adverse reactions have been associated with FYARRO in clinical trials and are discussed in greater detail in other sections of the label [see Warnings and Precautions (5)].

Stomatitis [see Warnings and Precautions (5.1)]

Myelosuppression [see Warnings and Precautions (5.2)]

Infections [see Warnings and Precautions (5.3)]

Hypokalemia [see Warnings and Precautions (5.4)]

Hyperglycemia [see Warnings and Precautions (5.5)]

Interstitial Lung Disease (ILD) / Non-Infectious Pneumonitis [see Warnings and Precautions (5.6)]

Hemorrhage [see Warnings and Precautions (5.7)]

Hypersensitivity [see Warnings and Precautions (5.8)]

6.1 Clinical Trials Experience

Because clinical trials are conducted under widely varying conditions, adverse reaction rates observed in the clinical trials of a drug cannot be directly compared to rates in the clinical trials of another drug and may not reflect the rates observed in practice.

The safety of FYARRO was assessed in a single-arm study (AMPECT). Thirty-four patients received FYARRO 100 mg/m^2 on Days 1 and 8 of 21-day cycles until disease progression or unacceptable toxicity [see Clinical Studies (14.1)]. Among the 34 patients who received FYARRO, 16 (47%) were exposed for 6 months or longer and 7 (21%) were exposed for greater than 1 year.

The median age of patients who received FYARRO was 59.5 years (range 27 to 78 years), 82% were female and Eastern Cooperative Oncology Group (ECOG) Performance Status was 0 (76%) or 1 (24%). Race was 71% White, 9% Black, 9% Asian, 3% Hawaiian/Pacific Islander and 9% Other/Not Reported. Ethnicity was 82% not Hispanic or Latino, 15% Hispanic or Latino, and 3% Not Reported.

Serious adverse reactions occurred in 14 (41%) patients who received FYARRO. Serious adverse reactions in >5% of patients, including 4 (12%) patients with infection and 2 (6%) patients each with abdominal pain, dehydration, and upper gastrointestinal hemorrhage. Fatal adverse reactions occurred in 1 (2.9%) patient who received FYARRO and experienced upper gastrointestinal hemorrhage.

Permanent discontinuation of FYARRO due to an adverse reaction occurred in 3 (9%) patients. Adverse reactions which resulted in permanent discontinuation of FYARRO included pneumonitis, anemia, and noninfective cystitis.

Dosage interruptions of FYARRO due to an adverse reaction occurred in 22 (65%) patients. Adverse reactions which required dosage interruption in >5% of patients included stomatitis in 6 (18%) patients, pneumonitis in 5 (15%) patients, anemia in 3 (9%) patients, and dehydration, dermatitis acneiform, and thrombocytopenia in 2 (6%) patients each.

Dose reductions of FYARRO due to an adverse reaction occurred in 12 (35%) patients. Adverse reactions which required dose reductions in >5% of patients included stomatitis and pneumonitis in 3 (9%) patients each.

The most common adverse reactions (≥30%) were stomatitis in 27 (79%) patients, fatigue and rash in 23 (68%) patients each, infection in 20 (59%) patients, nausea and edema in 17 (50%) patients each, diarrhea, musculoskeletal pain and decreased weight in 16 (47%) patients each, decreased appetite in 15 (44%) patients, cough in 12 (35%) patients, and vomiting and dysgeusia in 11 (32%) patients each. The most common Grade 3 to 4 laboratory abnormalities (≥6%) were decreased lymphocytes in 7 (21%) patients, increased glucose and decreased potassium in 4 (12%) patients each, decreased phosphate in 3 (9%) patients, and decreased hemoglobin and increased lipase in 2 (6%) patients each.

Table 4 summarizes the adverse reactions in AMPECT.

Table 4. Adverse Reactions ≥10% in Patients with PEComa Who Received FYARRO in AMPECT
 | FYARRO (N=34)
Adverse Reaction | All Grades (%) | Grade 3 to 4 [No Grade 4 reactions were reported] (%)
Gastrointestinal
Stomatitis [Includes stomatitis, aphthous ulcer, mouth ulceration, esophageal ulcer] | 79 | 18
Nausea | 50 | 0
Diarrhea [Includes diarrhea and enteritis] | 47 | 2.9
Vomiting | 32 | 2.9
Abdominal Pain [Includes abdominal pain, abdominal pain upper, and epigastric discomfort] | 29 | 6
Constipation | 24 | 2.9
Dry Mouth | 15 | 0
Hemorrhoids | 12 | 0
General disorders
Fatigue | 68 | 2.9
Edema [Includes face edema, generalized edema, edema, edema peripheral, and periorbital edema] | 50 | 2.9
Pyrexia | 24 | 0
Skin and subcutaneous tissue disorders
Rash [Includes dermatitis acneiform, palmar-plantar erythrodysesthesia syndrome, rash, rash erythematous, rash macular, rash maculo-papular, rash papular, rash pruritic, and skin exfoliation] | 68 | 0
Alopecia | 24 | 0
Pruritus | 18 | 0
Dry Skin | 12 | 0
Nail disorder | 12 | 0
Infections
Infections [Includes all reported infections, including but not limited to, upper respiratory tract infection, urinary tract infection, sinusitis , skin infection, folliculitis, nasopharyngitis, pharyngitis, pharyngitis streptococcal, pneumonia, vaginal infection] | 59 | 12
Metabolism and nutrition
Decreased appetite | 44 | 0
Dehydration | 15 | 6
Nervous system
Dysgeusia | 32 | 0
Headache | 29 | 0
Peripheral neuropathy [Includes dysesthesia, hypoesthesia, neuropathy peripheral, paresthesia, and peripheral sensory neuropathy] | 15 | 0
Dizziness [Includes dizziness, dizziness postural, and vertigo] | 12 | 0
Investigations
Weight decreased | 47 | 0
Musculoskeletal and connective tissue disorders
Musculoskeletal pain [Includes arthralgia, back pain, musculoskeletal chest pain, myalgia, neck pain, non-cardiac chest pain, pain in extremity] | 47 | 2.9
Respiratory, thoracic, and mediastinal disorders
Cough [Includes cough, productive cough, and upper-airway cough syndrome] | 35 | 0
Pneumonitis | 18 | 0
Dyspnea [Includes dyspnea and dyspnea exertional] | 12 | 0
Vascular disorders
Hypertension | 29 | 2.9
Hemorrhage [Includes epistaxis, hemorrhoidal hemorrhage, mouth hemorrhage, post procedural hemorrhage, and upper gastrointestinal hemorrhage. Includes one fatal adverse reaction of upper GI hemorrhage] | 24 | 2.9
Psychiatric disorders
Insomnia | 21 | 2.9
Eye disorders
Vision blurred | 12 | 0
Grading according to NCI CTCAE Version 4.03

Table 5 summarizes the laboratory abnormalities in AMPECT.

Table 5. Laboratory Abnormalities ≥10% That Worsened from Baseline in Patients with PEComa who Received FYARRO in AMPECT
 | FYARRO [The denominator used to calculate the rate varied from 33 to 34 based on the number of patients with a baseline value and at least one post-treatment value.] (N=34)
Laboratory Abnormality [Grading according to NCI CTCAE Version 4.03] | All Grades (%) | Grades 3 to 4 (%)
Hematology
Decreased lymphocytes | 82 | 21
Decreased hemoglobin | 68 | 6
Decreased leukocytes | 41 | 0
Decreased neutrophils | 35 | 0
Decreased platelets | 35 | 0
Chemistry
Increased creatinine | 82 | 0
Increased triglycerides | 52 | 0
Increased cholesterol | 48 | 3
Increased alanine aminotransferase (ALT) | 47 | 2.9
Decreased potassium | 44 | 12
Decreased magnesium | 42 | 0
Decreased albumin | 35 | 2.9
Increased aspartate transaminase (AST) | 32 | 2.9
Increased alkaline phosphatase | 29 | 0
Decreased sodium | 24 | 2.9
Decreased calcium | 15 | 0
Decreased glucose | 15 | 0
Decreased phosphate | 15 | 9
Increased lipase | 12 | 6
Increased glucose | 12 | 12
Increased sodium | 12 | 0

Clinically relevant adverse reactions occurring in <10% of patients included enteritis, edema, pancytopenia, acute kidney injury, and acute coronary syndrome.

7 DRUG INTERACTIONS

7.1 Effects of Other Drugs on FYARRO

CYP3A4 and/or P-gp Inhibitors or Inducers

CYP3A4 and/or P-gp inhibitors may increase sirolimus concentrations, which may increase the risk of FYARRO adverse reactions. CYP3A4 and/or P-gp inducers may decrease sirolimus concentrations, which may reduce FYARRO effectiveness.

- Strong CYP3A4 and/or P-gp Inhibitors or Inducers: Avoid concomitant use of FYARRO with strong CYP3A4 and/or P-gp inhibitors or strong CYP3A4 and/or P-gp inducers [see Dosage and Administration (2.3), Clinical Pharmacology (12.3)].
- Grapefruit or Grapefruit Juice: Avoid concomitant use of FYARRO with grapefruit or grapefruit juice.
- Moderate or Weak CYP3A4 Inhibitors: Reduce the dosage of FYARRO when used concomitantly with a moderate or weak CYP3A4 inhibitor [see Dosage and Administration (2.3), Clinical Pharmacology (12.3)].
- Moderate or Weak CYP3A4 Inducers: Use of FYARRO may result in decreased effectiveness.

8 USE IN SPECIFIC POPULATIONS

8.1 Pregnancy

Risk Summary

Based on animal studies and the mechanism of action, FYARRO can cause fetal harm when administered to a pregnant woman [see Clinical Pharmacology (12.1)]. Although there are no data on the use of FYARRO in pregnant women, there are limited data on the use of sirolimus during pregnancy. In animal studies, oral sirolimus was embryo/fetotoxic in rats [see Data] at sub-therapeutic doses. Advise pregnant women of the potential risk to a fetus.

The estimated background risk of major birth defects and miscarriage for the indicated population is unknown. In the U.S. general population, the estimated background risk of major birth defects and miscarriage in clinically recognized pregnancies is 2-4% and 15-20%, respectively.

Data

Animal Data

Reproductive studies in animals have not been performed with FYARRO. Studies with an oral formulation of sirolimus have shown that it crosses the placenta and is toxic to the conceptus.

In rat embryo-fetal development studies, pregnant rats were administered an oral formulation of sirolimus during the period of organogenesis (Gestational Day 6-15). Sirolimus produced embryo-fetal lethality at 0.5 mg/kg and reduced fetal weight at 1 mg/kg. The no observed adverse effect level (NOAEL) for fetal toxicity in rats was 0.1 mg/kg. Maternal toxicity (weight loss) was observed at 2 mg/kg. The NOAEL for maternal toxicity was 1 mg/kg.

In rabbit embryo-fetal development studies, pregnant rabbits were administered an oral formulation of sirolimus during the period of organogenesis (Gestational Day 6-18). There were no effects on embryo-fetal development at doses up to 0.05 mg/kg; however, at doses of 0.05 mg/kg and above, the ability to sustain a pregnancy was impaired (i.e., embryo-fetal abortion or early resorption). Maternal toxicity (decreased body weight) was observed at 0.05 mg/kg. The NOAEL for maternal toxicity was 0.025 mg/kg.

In a pre- and post-natal development study in rats, pregnant females were dosed with an oral formation of sirolimus during gestation and lactation (Gestational Day 6 through Lactation Day 20). An increased incidence of dead pups occurred at 0.5 mg/kg, resulting in reduced live litter size. At 0.1 mg/kg, there were no adverse effects on offspring. Sirolimus did not cause maternal toxicity or affect developmental parameters in the surviving offspring (e.g., morphological development, motor activity, learning, or fertility assessment) at 0.5 mg/kg, the highest oral dose tested.

8.2 Lactation

Risk Summary

There are no data on the presence of FYARRO in human milk or its effects on the breastfed child or on milk production.

It is not known whether sirolimus is present in human milk. There are no data on its effects on the breastfed infant or milk production. The pharmacokinetic and safety profiles of sirolimus in infants are not known. Sirolimus is present in the milk of lactating rats. There is potential for serious adverse effects from sirolimus in breastfed infants based on mechanism of action [see Clinical Pharmacology (12.1)]. Because of the potential for serious adverse reactions in breastfed infants from FYARRO, advise women not to breastfeed during treatment with FYARRO and for 2 weeks after the last dose.

8.3 Females and Males of Reproductive Potential

FYARRO can cause fetal harm when administered to a pregnant woman [see Warnings and Precautions (5.9), Use in Specific Populations (8.1)].

Pregnancy Testing

Verify pregnancy status of females of reproductive potential prior to initiating FYARRO.

Contraception

Females

Advise females of reproductive potential to use effective contraception during treatment with FYARRO and for 12 weeks after the last dose.

Males

Advise males with female partners of reproductive potential to use effective contraception during treatment with FYARRO and for 12 weeks after the last dose.

Infertility

Although there are no data on the impact of FYARRO on fertility, based on available clinical findings with oral formulation of sirolimus and findings in animals, male and female fertility may be compromised by the treatment with FYARRO [see Warnings and Precautions (5.10), Nonclinical Toxicology (13.1)]. Ovarian cysts and menstrual disorders (including amenorrhea and menorrhagia) have been reported in females with the use of oral formulation of sirolimus. Azoospermia has been reported in males with the use of oral formulation sirolimus and has been reversible upon discontinuation in most cases.

8.4 Pediatric Use

The safety and efficacy of FYARRO in pediatric patients have not been established.

8.5 Geriatric Use

Of the 34 patients treated with FYARRO, 44% were 65 years of age and older, and 6% were 75 years of age and older. Clinical studies of FYARRO did not include sufficient numbers of patients aged 65 and over to determine whether they respond differently from younger patients.

8.6 Hepatic Impairment

FYARRO is not recommended for use in patients with severe hepatic impairment. Reduce FYARRO dosage in patients with mild or moderate hepatic impairment [see Dosage and Administration (2.4), Clinical Pharmacology (12.3)].

11 DESCRIPTION

FYARRO (sirolimus protein-bound particles for injectable suspension) (albumin-bound) is sirolimus formulated as albumin-bound nanoparticles. The active ingredient in FYARRO is sirolimus bound to albumin which exists in the nanoparticles in a non-crystalline, amorphous state.

Sirolimus is a mechanistic target of rapamycin kinase (mTOR) inhibitor. Sirolimus is a macrocyclic lactone produced by Streptomyces hygroscopicus. The chemical name of sirolimus is [3S[3R*[S*(1R*,3S*,4S*)),6S*,7E,9S*,10S*,12S*,14R*,15E,17E,19E,21R*,23R*,26S*, 27S*,3 4aR*]]- 9,10,12,13,14,21,22,23,24,25,26,27,32,33,34,34a-Hexadecahydro-9,27-dihydroxy 3-[2-(4-hydroxy-3- methoxycyclohexyl)-1-methylethyl]-10,21-dimethoxy-6,8,12,14,20,26-hexamethyl-23,27-epoxy-3H- pyrido[2,1-c][1,4]oxaazacyclohentriacontine-1,5,11,28,29(4H,6H,31H)-pentone. Its empirical formula is C51H79NO13, and the molecular weight is 914.2. The structural formula of sirolimus is illustrated as follows:

Sirolimus is a white to off-white crystalline powder and is insoluble in water but freely soluble in benzyl alcohol, chloroform, acetone, and acetonitrile.

FYARRO is supplied as a white to yellow, sterile, lyophilized powder for reconstitution with 20 mL of 0.9% Sodium Chloride Injection, USP prior to intravenous infusion. Each single-dose vial contains 100 mg of sirolimus (bound to human albumin) and approximately 850 mg of human albumin (containing sodium caprylate and sodium acetyltryptophanate). Each milliliter (mL) of reconstituted suspension contains 5 mg sirolimus formulated as albumin-bound particles.

12 CLINICAL PHARMACOLOGY

12.1 Mechanism of Action

Sirolimus in FYARRO is an inhibitor of mechanistic target of rapamycin kinase (mTOR, previously known as mammalian target of rapamycin). mTOR, a serine threonine kinase, is downstream of the PI3K/AKT pathway, controls key cellular processes such as cell survival, growth, and proliferation, and is commonly dysregulated in several human cancers. In cells, sirolimus binds to the immunophilin, FK Binding Protein-12 (FKBP-12), to generate an immunosuppressive complex. The sirolimus-FKBP-12 complex binds to and inhibits activation of the mechanistic target of rapamycin complex 1 (mTORC1). Inhibition of mTOR by sirolimus has been shown to reduce cell proliferation, angiogenesis, and glucose uptake in in vitro and in vivo studies. In a nonclinical study in athymic mice bearing human tumor xenografts, intravenous administration of FYARRO resulted in higher tumor accumulation of sirolimus, inhibition of an mTOR target in the tumor, and tumor growth inhibition compared to administration of an oral formulation of sirolimus at the same weekly total dose.

12.2 Pharmacodynamics

Sirolimus exposure-response relationship has not been fully characterized.

Cardiac Electrophysiology

The effect of FYARRO on the QTc interval has not been adequately characterized.

12.3 Pharmacokinetics

Absorption

Following administration of FYARRO at the recommended dosage, the estimated mean (%CV) Cmax and AUC0-inf of sirolimus in patients with advanced solid tumors were 2590 ng/mL (30% CV) and 22100 ng∙h/mL (50% CV), respectively.

Distribution

The protein binding of sirolimus is >99%, primarily to serum albumin in vitro.

Elimination

The mean elimination half-life of sirolimus is approximately 59 hours (41% CV).

Metabolism

Sirolimus is metabolized by CYP3A4.

Excretion

Following a single radiolabeled sirolimus oral dose to human subjects, 91% and 2% of the radioactivity was recovered in feces and urine, respectively.

Specific Populations

There were no clinically significant differences in the pharmacokinetics of sirolimus based on age (18 to 78 years), sex, mild or moderate renal impairment (creatinine clearance 30 to 89 mL/min). The effect of race, severe renal impairment, and hepatic impairment on the pharmacokinetics of sirolimus is unknown.

Drug Interaction Studies

No studies evaluating the drug interaction potential of FYARRO have been conducted.

Sirolimus is a substrate for both CYP3A4 and P-gp.

13 NONCLINICAL TOXICOLOGY

13.1 Carcinogenesis, Mutagenesis, Impairment of Fertility

No carcinogenicity, mutagenesis, or fertility studies were conducted with FYARRO.

Carcinogenicity studies have been conducted in mice and rats with an oral formulation of sirolimus. In an 86-week female mouse study, there was a statistically significant increase in malignant lymphoma at all dose levels compared with controls. In a second mouse study, hepatocellular adenoma and carcinoma in males were considered sirolimus-related. In a 104-week rat study, there were no significant findings.

Sirolimus was not genotoxic in an in vitro bacterial reverse mutation assay, a Chinese hamster ovary cell chromosomal aberration assay, a mouse lymphoma cell forward mutation assay, or an in vivo mouse micronucleus assay.

When female rats were treated by gavage with an oral formulation of sirolimus and mated to untreated males, female fertility was decreased at 0.5 mg/kg due to decreased implantation. In addition, reduced ovary and uterus weight were observed. The NOAEL for female rat fertility was 0.1 mg/kg.

When male rats were treated by gavage with an oral formulation of sirolimus and mated to untreated females, male fertility was decreased at 2 mg/kg. Atrophy of testes, epididymides, prostate, seminiferous tubules, and reduced sperm counts were observed. The NOAEL for male rat fertility was 0.5 mg/kg.

Testicular tubular degeneration was also seen in a 4-week intravenous study of sirolimus in monkeys at 0.1 mg/kg.

14 CLINICAL STUDIES

14.1 Perivascular Epithelioid Cell Tumor (PEComa)

The efficacy of FYARRO was assessed in AMPECT (NCT02494570), a multi-center, single-arm clinical trial in 31 patients with locally advanced unresectable or metastatic malignant PEComa. Patients were required to have measurable disease at baseline, centrally confirmed diagnosis by pathology of malignant PEComa, and Eastern Cooperative Oncology Group (ECOG) Performance Status (PS) of 0 or 1. Patients with lymphangioleiomyomatosis and prior treatment with a mTOR inhibitor were excluded. Patients received FYARRO at a dose of 100 mg/m^2 on Days 1 and 8 of 21-day cycles until disease progression or unacceptable toxicity.

The efficacy population of 31 patients had the following demographic characteristics: median age 60 years (range 34 to 78), 81% Female, 74% White, 10% Black, and 81% ECOG PS of 0. Five (16%) patients had locally advanced disease and 26 (84%) had metastatic disease. Ninety-four percent of patients had prior surgery,19% had prior radiation therapy, and 13% had prior systemic therapy.

The major efficacy outcome measures were overall response rate (ORR) and duration of response (DOR) as assessed by blinded independent central review (BICR) using RECIST v.1.1.

The efficacy results are summarized in Table 6.

Table 6. Efficacy Results in AMPECT
Efficacy Endpoints | FYARRO (N=31)
Overall Response Rate (95% CI) [All responses were initially partial responses. Two patients with partial response converted to complete response during the follow up-period.] | 39% (22%, 58%)
Duration of Response (DOR) | (N=12)
Median (95% CI) in months | NR (6.5, NE)
Range in months | 5.6, 55.5 [Denotes ongoing responses]
% with duration ≥6 months | 92%
% with duration ≥12 months | 67%
% with duration ≥24 months | 58%
CI = Confidence Interval; NR = Not Reached; NE = Not Estimable

15 REFERENCES

1. OSHA Hazardous Drugs. OSHA. https://www.osha.gov/SLTC/hazardousdrugs/index.html.

16 HOW SUPPLIED/STORAGE AND HANDLING

FYARRO (sirolimus protein-bound particles for injectable suspension) (albumin-bound) is a white to yellow, sterile lyophilized powder supplied as:

NDC 80803-153-50, 100 mg of sirolimus in a single-dose vial. Each carton contains 1 vial.

Store the vials in the original cartons at 2° to 8°C [USP Refrigerated Temperature] (36° to 46°F).

Retain in the original package to protect from light.

FYARRO is a hazardous drug. Follow applicable special handling and disposal procedures.^1

17 PATIENT COUNSELING INFORMATION

Stomatitis

Advise patients of the risk of stomatitis [see Warnings and Precautions (5.1)].

Myelosuppression

Advise patients of the risk of myelosuppression and the need to monitor blood counts periodically during therapy [see Warnings and Precautions (5.2)].

Infections

Advise patients that they are more susceptible to infections and that they should immediately report any signs or symptoms of infection to their healthcare provider [see Warnings and Precautions (5.3)].

Hypokalemia

Advise patients of the risk of hypokalemia and the need to monitor potassium periodically during therapy [see Warnings and Precautions (5.4)].

Hyperglycemia

Advise patients of the risk of hyperglycemia and the need to monitor glucose periodically during therapy [see Warnings and Precautions (5.5)].

Interstitial Lung Disease / Non-Infectious Pneumonitis

Advise patients of the risk of developing non-infectious pneumonitis and to immediately report any new or worsening respiratory symptoms to their healthcare provider [see Warnings and Precautions (5.6)].

Hemorrhage

Advise patients of the risk of hemorrhage. Instruct patients to report signs of bleeding, and to seek immediate medical attention for signs or symptoms of severe bleeding [see Warnings and Precautions (5.7)].

Hypersensitivity Reactions

Advise patients of the risk of clinically significant hypersensitivity reactions and to promptly contact their healthcare provider or seek emergency care for signs of hypersensitivity reaction including rash, itching, hives, difficulty breathing or swallowing, flushing, chest pain, or dizziness [see Contraindications (4), Warnings and Precautions (5.8)].

Embryo-Fetal Toxicity

Advise females of reproductive potential of the potential risk to a fetus and to inform their healthcare provider of a known or suspected pregnancy [see Warnings and Precautions (5.9)]. Advise females of reproductive potential to use effective contraception during treatment and for 12 weeks after the last dose [see Use in Specific Populations (8.1, 8.3)].

Advise males with female partners of reproductive potential to use effective contraception during treatment and for 12 weeks after the last dose [see Warnings and Precautions (5.9), Use in Specific Populations (8.3)].

Infertility

Advise males and females of reproductive potential of the potential risk for impaired fertility [see Warnings and Precautions (5.10), Use in Specific Populations (8.3)].

Immunizations

Advise patients that vaccinations may be less effective while being treated with FYARRO. Advise patients to avoid the use of live vaccines, and close contact with those who have received live vaccines, while on FYARRO [see Warnings and Precautions (5.11)].

Lactation

Advise women not to breastfeed during treatment with FYARRO and for 2 weeks after the last dose [see Use in Specific Populations (8.2)].

Drug Interactions

Advise patients to inform their healthcare provider about all concomitant medications, including prescription medicine, over the counter drugs, vitamins, and herbal products [see Drug Interactions (7)]. Inform patients to avoid grapefruit and grapefruit juice while taking FYARRO.

This product's label may have been updated. For current full prescribing information, please visit www.aadibio.com.

Manufactured for Aadi Bioscience, Inc., Pacific Palisades, CA 90272.

FYARRO is a trademark of Aadi Bioscience, Inc.

Patent: www.aadibio.com/patents/

PRINCIPAL DISPLAY PANEL

NDC 80803-153-50 Rx Only
Fyarro™
sirolimus protein-bound
particles for injectable
suspension (albumin-bound)
100 mg per vial
For intravenous infusion
Single-dose vial
Discard any unused portion.